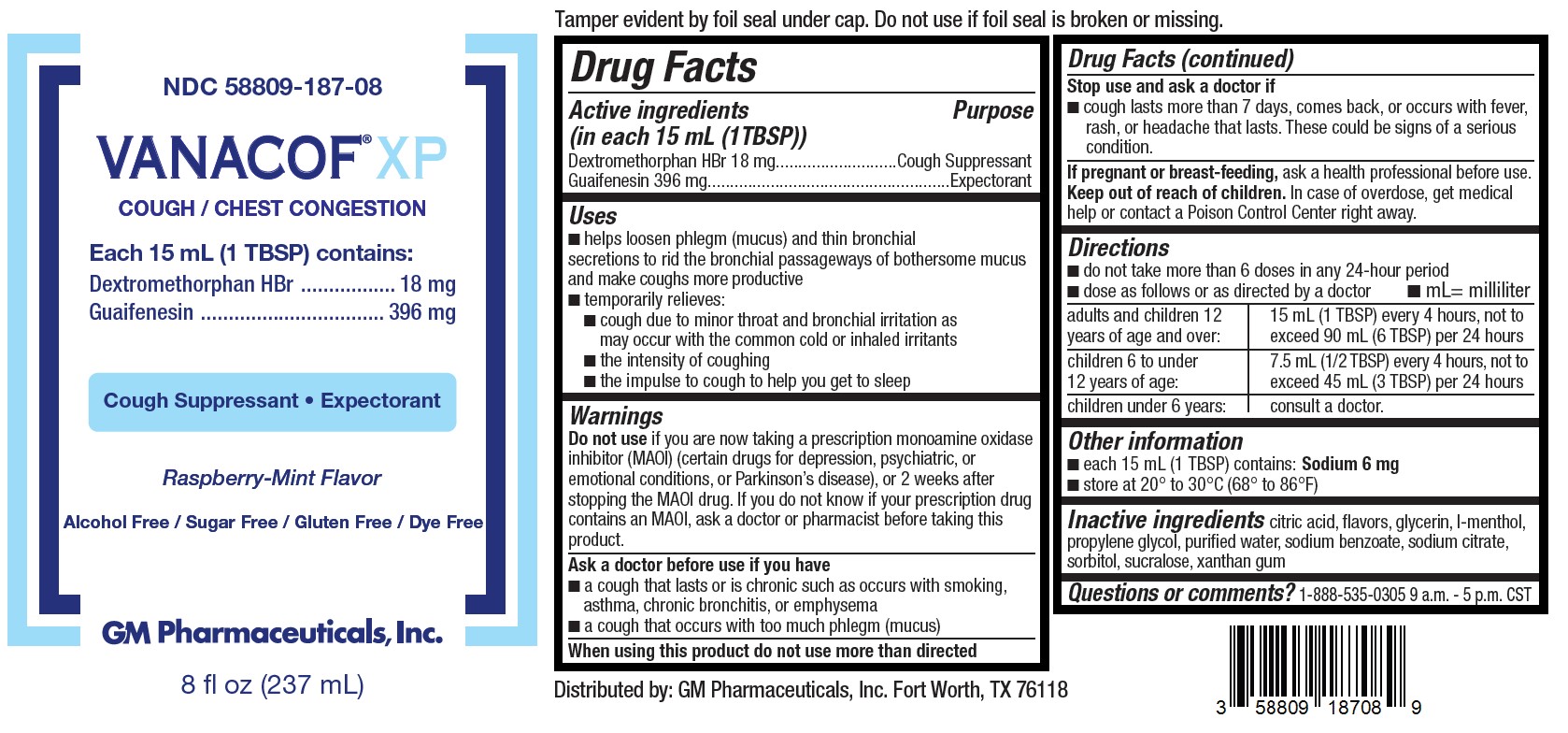 DRUG LABEL: VANACOF XP Cough / Chest Congestion
NDC: 58809-187 | Form: SOLUTION
Manufacturer: GM Pharmaceuticals, INC
Category: otc | Type: HUMAN OTC DRUG LABEL
Date: 20260108

ACTIVE INGREDIENTS: GUAIFENESIN 396 mg/15 mL; DEXTROMETHORPHAN HYDROBROMIDE 18 mg/15 mL
INACTIVE INGREDIENTS: SODIUM CITRATE; MENTHOL; XANTHAN GUM; SORBITOL; SODIUM BENZOATE; ANHYDROUS CITRIC ACID; GLYCERIN; SUCRALOSE; PROPYLENE GLYCOL; WATER

VANACOF XP Cough / Chest Congestion

Active Ingredients (in each 15 mL (1TBSP))

Dextromethorphan HBr 18 mg

Guaifenesin 396 mg

Purpose

Cough Suppressant

Expectorant

Uses

- ■ helps loosen phlegm (mucus) and thin bronchial secretions to rid the bronchial passageways of bothersome mucus and make coughs more productive
- ■ temporarily relieves:

■ cough due to minor throat and bronchial irritation as may occur with the common cold or inhaled irritants

■ the intensity of coughing

■ the impulse to cough to help you get to sleep

Warnings

Do not use

if you are now taking a prescription monoamine oxidase inhibitor (MAOI) (certain drugs for depression, psychiatric, or emotional conditions, or Parkinson’s disease), or 2 weeks after stopping the MAOI drug. If you do not know if your prescription drug contains an MAOI, ask a doctor or pharmacist before taking this product.

Ask a doctor before use if you have

- ■ a cough that lasts or is chronic such as occurs with smoking, asthma, chronic bronchitis, or emphysema
- ■ a cough that occurs with too much phlegm (mucus)

When using this product

do not use more than directed

Stop use and ask a doctor if

■ cough lasts more than 7 days, comes back, or occurs with fever, rash, or headache that lasts. These could be signs of a serious condition.

If pregnant or breast-feeding,

ask a health professional before use.

Keep out of reach of children.

In case of overdose, get medical help or contact a Poison Control Center right away.

Directions

- ■ do not take more than 6 doses in any 24-hour period
- ■ dose as follows or as directed by a doctor ■ mL= milliliter

adults and children 12 years of age and over: | 15 mL (1 TBSP) every 4 hours, not to exceed 90 mL (6 TBSP) per 24 hours
children 6 to under 12 years of age: | 7.5 mL (1/2 TBSP) every 4 hours, not to exceed 45 mL (3 TBSP) per 24 hours
children under 6 years: | consult a doctor.

Other information

■ each 15 mL (1 TBSP) contains: Sodium 6 mg

STORAGE AND HANDLING

■ store at 20° to 30°C (68° to 86°F)

Inactive ingredients

citric acid, flavors, glycerin, l-menthol, propylene glycol, purified water, sodium benzoate, sodium citrate, sorbitol, sucralose, xanthan gum

Questions or comments?

1-888-535-0305 9 a.m. - 5 p.m. CST

Tamper evident by foil seal under cap. Do no use if foil seal is broken or missing.

Distributed by: GM Pharmaceuticals, Inc. Fort Worth, TX 76118

PACKAGE LABEL

NDC 58809-187-08

VANACOF® XP

COUGH / CHEST CONGESTION

Each 15 mL (1 TBSP) contains:

Dextromethorphan HBr.....18 mg

Guaifenesin ....................396 mg

Cough Suppressant ■ Expectorant

Raspberry-Mint Flavor

Alcohol Free / Sugar Free / Gluten Free / Dye Free